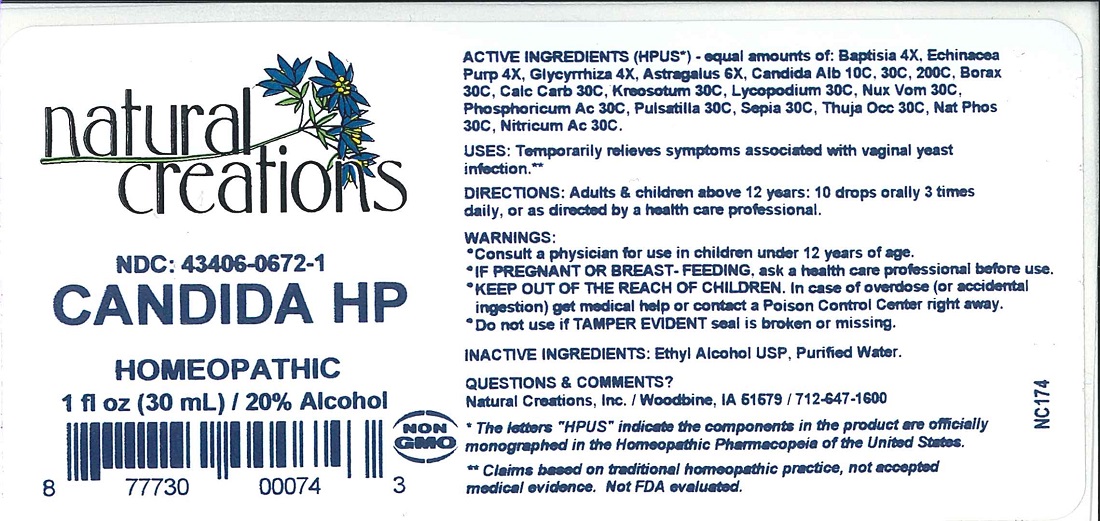 DRUG LABEL: Candida HP
NDC: 43406-0672 | Form: LIQUID
Manufacturer: Natural Creations, Inc.
Category: homeopathic | Type: HUMAN OTC DRUG LABEL
Date: 20251120

ACTIVE INGREDIENTS: BAPTISIA TINCTORIA ROOT 4 [hp_X]/1 mL; ECHINACEA PURPUREA 4 [hp_X]/1 mL; GLYCYRRHIZA GLABRA 4 [hp_X]/1 mL; ASTRAGALUS NUTTALLII LEAF 6 [hp_X]/1 mL; SODIUM BORATE 30 [hp_C]/1 mL; OYSTER SHELL CALCIUM CARBONATE, CRUDE 30 [hp_C]/1 mL; WOOD CREOSOTE 30 [hp_C]/1 mL; LYCOPODIUM CLAVATUM SPORE 30 [hp_C]/1 mL; SODIUM PHOSPHATE, DIBASIC, HEPTAHYDRATE 30 [hp_C]/1 mL; NITRIC ACID 30 [hp_C]/1 mL; STRYCHNOS NUX-VOMICA SEED 30 [hp_C]/1 mL; PHOSPHORIC ACID 30 [hp_C]/1 mL; PULSATILLA VULGARIS 30 [hp_C]/1 mL; SEPIA OFFICINALIS JUICE 30 [hp_C]/1 mL; THUJA OCCIDENTALIS LEAFY TWIG 30 [hp_C]/1 mL; CANDIDA ALBICANS 200 [hp_C]/1 mL
INACTIVE INGREDIENTS: WATER; ALCOHOL

CANDIDA HP

ACTIVE INGREDIENT

ACTIVE INGREDIENTS (HPUS*) - equal amounts of: Baptisia 4X, Echinacea Purp 4X, Glycyrrhiza 4X, Astragalus 6X, Candida Alb 10C, 30C, 200C, Borax 30C, Calc Carb 30C, Kreosotum 30C, Lycopodium 30C, Nux Vom 30C, Phosphoricum Ac 30C, Pulsatilla 30C, Sepia 30C, Thuja Occ 30C, Nat Phos 30C, Nitricum Ac 30C.

INDICATIONS AND USAGE

USES: Temporarily relieves symptoms associated with vaginal yeast infection.**

WARNINGS:

- Consult a physician for use in children under 12 years of age.
- IF PREGNANT OR BREAST-FEEDING, ask a health care professional before use.
- KEEP OUT OF THE REACH OF CHILDREN. In case of overdose (or accidental ingestion) get medical help or contact a Poison Control Center right away.
- Do not use if TAMPER EVIDENT seal is broken or missing.

DOSAGE AND ADMINISTRATION

DIRECTIONS: Adults & children above 12 years: 10 drops orally 3 times daily, or as directed by a health care professional.

REFERENCES

*The letters "HPUS" indicate the components in the product are officially monographed in the Homeopathic Pharmacopeia of the United States.

** Claims based on traditional homeopathic practice, not accepted medical evidence. Not FDA evaluated.

INACTIVE INGREDIENTS: Ethyl Alcohol USP, Purified Water.

QUESTIONS AND COMMENTS?

Natural Creations / Woodbine, IA / 51579 712-647-2780

PURPOSE

USES: Temporarily relieves symptoms associated with vaginal yeast infection.**

KEEP OUT OF REACH OF CHILDREN

KEEP OUT OF THE REACH OF CHILDREN. In case of overdose (or accidental ingestion) get medical help or contact a Poison Control Center.

PACKAGE LABEL

NDC: 43406-0672-1

CANDIDA HP

HOMEOPATHIC

1 fl oz (30 mL) / 20% Alcohol

UPC: 877730000743 NON GMO Logo